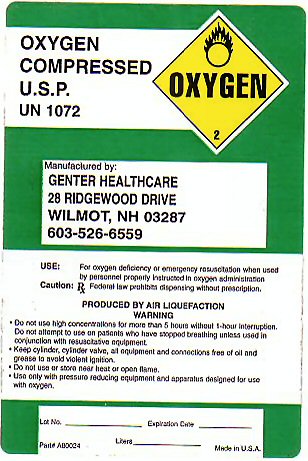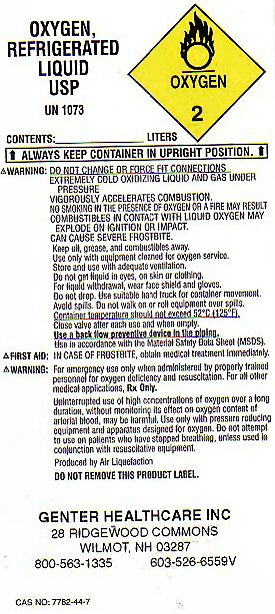 DRUG LABEL: OXYGEN
NDC: 65248-001 | Form: GAS
Manufacturer: Genter Healthcare, Inc
Category: prescription | Type: HUMAN PRESCRIPTION DRUG LABEL
Date: 20181231

ACTIVE INGREDIENTS: OXYGEN 99 L/100 L

OXYGEN COMPRESSED LABEL

OXYGEN COMPRESSED U.S.P. UN 1072 OXYGEN-2 USE: FOR OXYGEN DEFICIENCY OR EMERGENCY RESUSCITATION WHEN USED BY PERSONNEL PROPERLY INSTRUCTED IN OXYGEN ADMINISTRATION. CAUTION: FEDERAL LAW PROHIBITS DISPENSING WITHOUT PRESCRIPTION. PRODUCED BY AIR LIQUEFACTION.

WARNING: DO NOT USE HIGH CONCENTRATIONS FOR MORE THAN 5 HOURS WITHOUT 1 HOUR INTERRUPTION. DO NOT ATTEMPT TO USE ON PATIENTS WHO HAVE STOPPED BREATHING UNLESS USED IN CONJUNCTION WITH RESUSCITATIVE EQUIPMENT. KEEP CYLINDER, CYLINDER VALVE, ALL EQUIPMENT AND CONNECTIONS FREE OF OIL AND GREASE TO AVOID VIOLENT IGNITION. DO NOT USE OR STORE NEAR HEAT OR OPEN FLAME. USE ONLY WITH PRESSURE REDUCING EQUIPMENT AND APPARATUS DESIGNED FOR USE WITH OXYGEN.

LOT NO. ___________ EXPIRATION DATE____________ LITERS__________ PART# A80024 MADE IN USA.

OXYGEN REFRIGERATED LIQUID LABEL

OXYGEN REFRIGERATED LIQUID USP UN 1073 OXYGEN-2 CONTENTS______LITERS ALWAYS KEEP CONTAINER IN UPRIGHT POSITION. WARNING: DO NOT CHANGE OR FORCE FIT CONNECTIONS. EXTREMELY COLD OXIDIZING LIQUID AND GAS UNDER PRESSURE. VIGOROUSLY ACCELERATES COMBUSTION. NO SMOKING IN THE PRESENCE OF OXYGEN OR A FIRE MAY RESULT. COMBUSTIBLES IN CONTACT WITH LIQUID OXYGEN MAY EXPLODE ON IGNITION OR IMPACT. CAN CAUSE SEVERE FROSTBITE. KEEP OIL, GREASE, AND COMBUSTIBLES AWAY. USE ONLY WITH EQUIPMENT CLEANED FOR OXYGEN SERVICE. STORE AND USE WITH ADEQUATE VENTILATION. DO NOT GET LIQUID IN EYES, ON SKIN OR CLOTHING. FOR LIQUID WITHDRAWAL WEAR FACE SHIELD AND GLOVES. DO NOT DROP. USE SUITABLE HAND TRUCK FOR CONTAINER MOVEMENT. AVOID SPILLS. DO NOT WALK ON OR ROLL EQUIPMENT OVER SPILLS. CONTAINER TEMPERATURE SHOULD NOT EXCEED 52C (125 F) CLOSE VALVE AFTER EACH USE AND WHEN EMPTY. USE A BACK FLOW PREVENTATIVE DEVICE IN THE PIPING. USE IN ACCORDANCE WITH MATERIAL SAFETY DATA SHEET (MSDS) FIRST AID: IN CASE OF FROSTBITE OBTAIN MEDICAL TREATMENT IMMEDIATELY.

WARNING: FOR EMERGENCY USE ONLY WHEN ADMINISTERED BY PROPERLY TRAINED PERSONNEL FOR OXYGEN DEFICIENCY AND RESUSCITATION. FOR ALL OTHER MEDICAL APPLICATIONS Rx ONLY. UNINTERRUPTED USE OF HIGH CONCENTRATIONS OF OXYGEN OVER A LONG DURATION WITHOUT MONITORING ITS EFFECT ON OXYGEN CONTENT OF ARTERIAL BLOOD MAY BE HARMFUL. USE ONLY WITH PRESSURE REDUCING EQUIPMENT AND APPARATUS DESIGNED FOR OXYGEN. DO NOT ATTEMPT TO USE ON PATIENTS WHO HAVE STOPPED BREATHING, UNLESS USED IN CONJUNCTION WITH RESUSCITATIVE EQUIPMENT. PRODUCED BY AIR LIQUEFACTION. DO NOT REMOVE THIS PRODUCT LABEL. CAS NO 7782-44-7